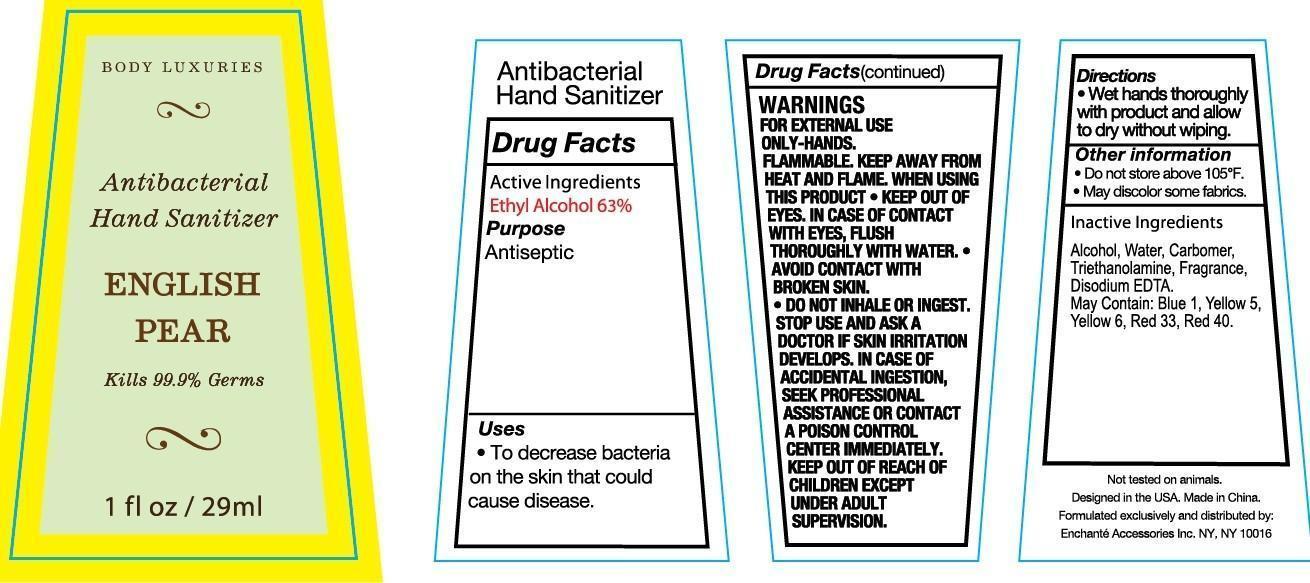 DRUG LABEL: Body Luxuries English Pear Antibacterial Hand Sanitizer
NDC: 50563-128 | Form: LIQUID
Manufacturer: ENCHANTE ACCESSORIES INC. 
Category: otc | Type: HUMAN OTC DRUG LABEL
Date: 20121222

ACTIVE INGREDIENTS: ALCOHOL 63 mL/100 mL
INACTIVE INGREDIENTS: WATER 36.11 mL/100 mL; CARBOMER COPOLYMER TYPE A; TROLAMINE; EDETATE DISODIUM; D&C RED NO. 33; FD&C BLUE NO. 1; FD&C YELLOW NO. 5; FD&C YELLOW NO. 6; FD&C RED NO. 40

Drug Fact

Active Ingredient

Ethyl Alcohol 63%

Purpose

Antiseptic

Uses

To decrease bacteria on the skin that could cause diseases

WARNINGS

For external use only-hands

Flammable: Keep away from heat and flame

When using this product: Keep out of eyes. In case of contact with eyes, flush thoroughly with water. Avoid Contact with broken skin. Do not inhale or ingest.

Stop use and ask a doctor if skin irritation develops

Keep out of reach of children. In case of accidental ingestion, seek professional assistance or contact a Poison Control Center immediately

Directions

- Wet hands thoroughly with product and allow to dry without wiping

Other Information:

- Do not store above 105F
- May discolor some fabrics

Inactive Ingredient:

Deionized Water, Triethanolamine, Carbomer, Fragrance, Disodium EDTA, may contain D and C Red No. 33, FD and C Red No. 40, FD and C Blue No. 1, FD and C Yellow No. 5, FD and C Yellow No. 6.

PACKAGE LABEL

lab